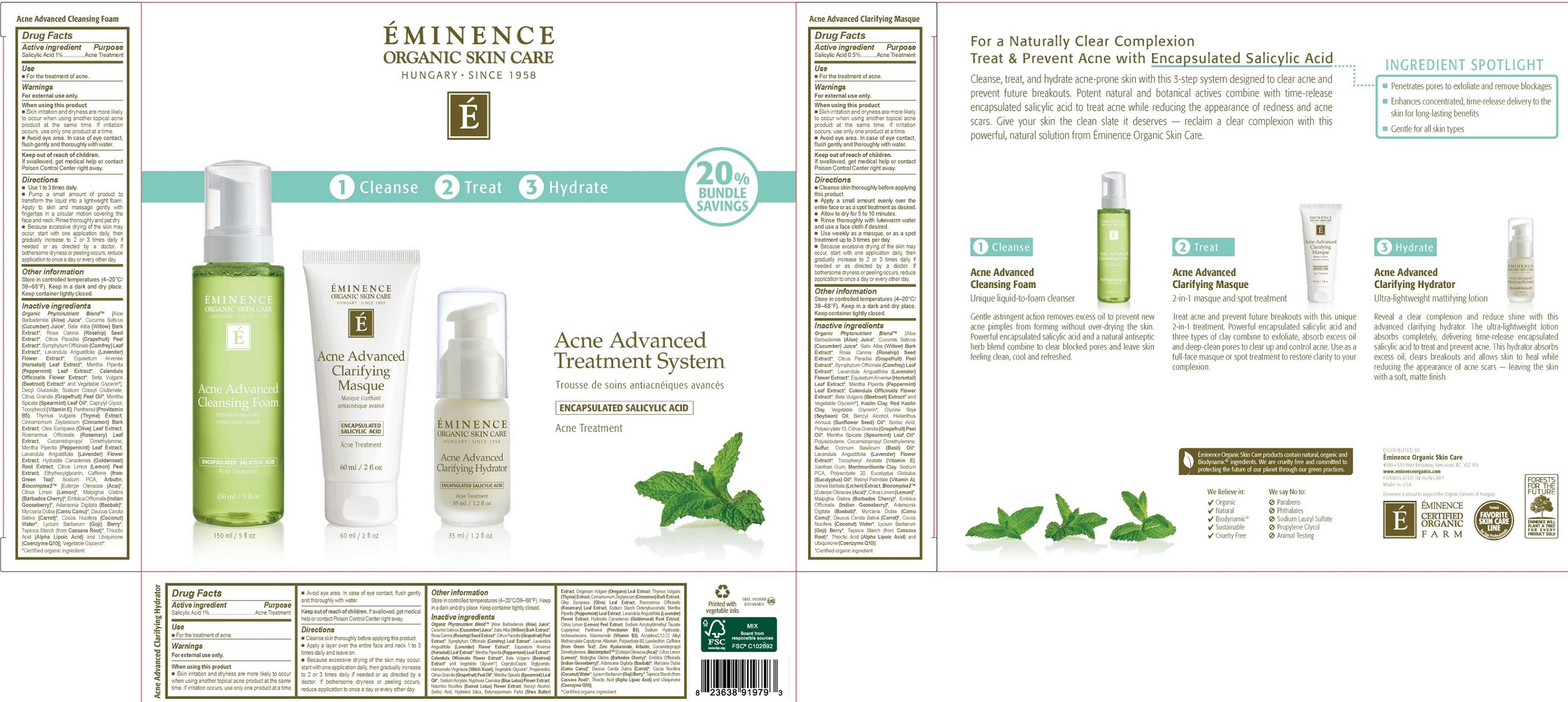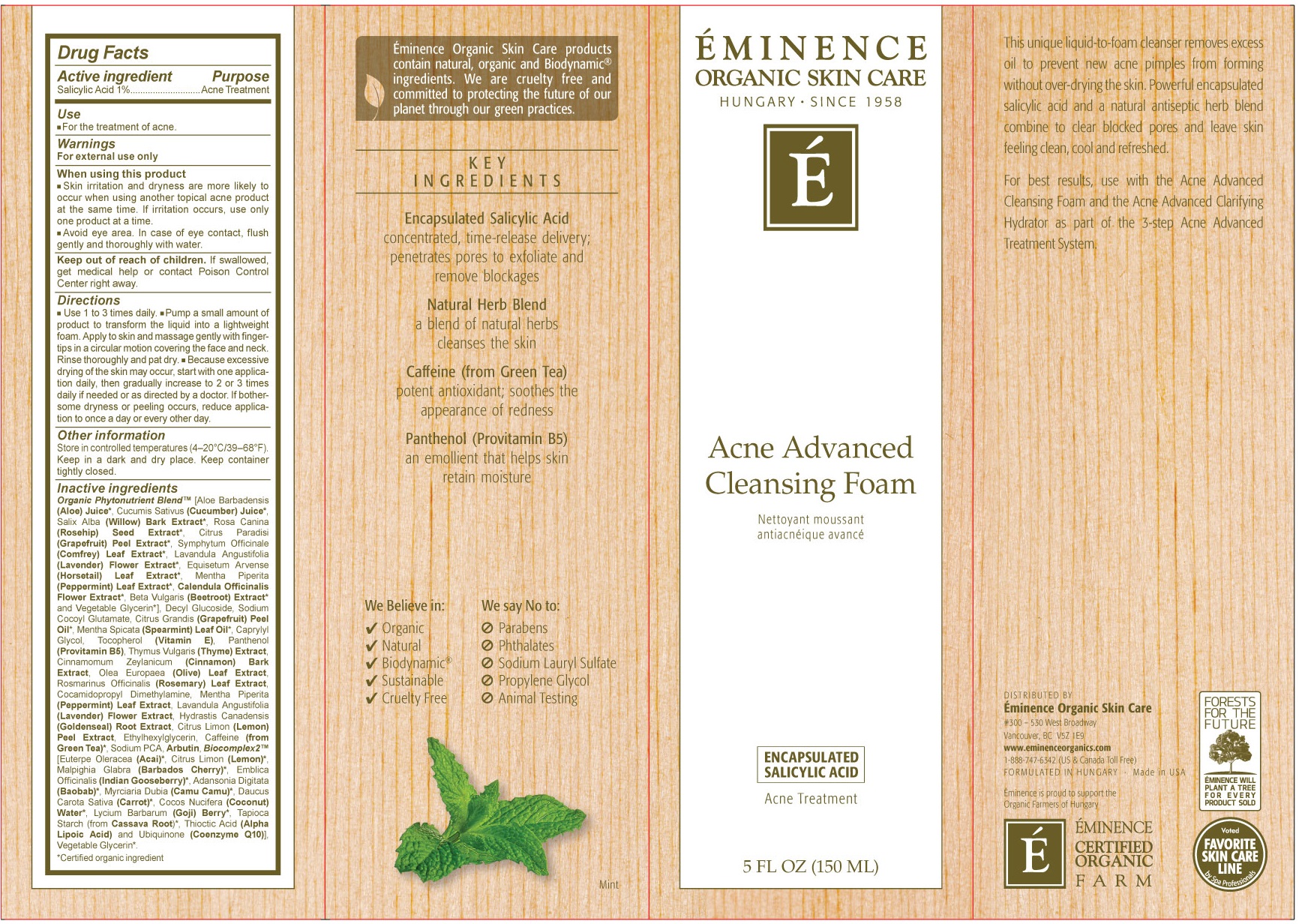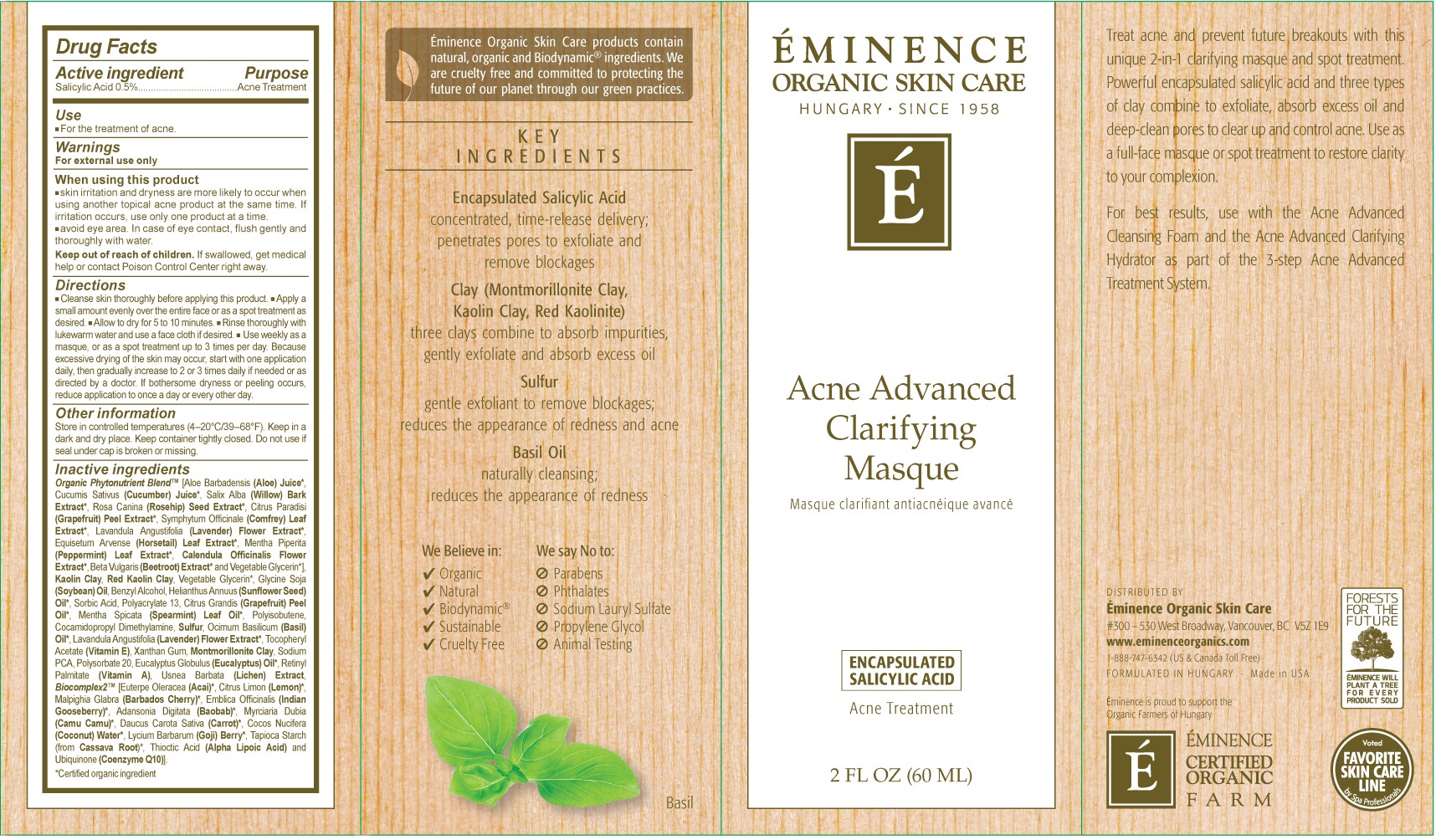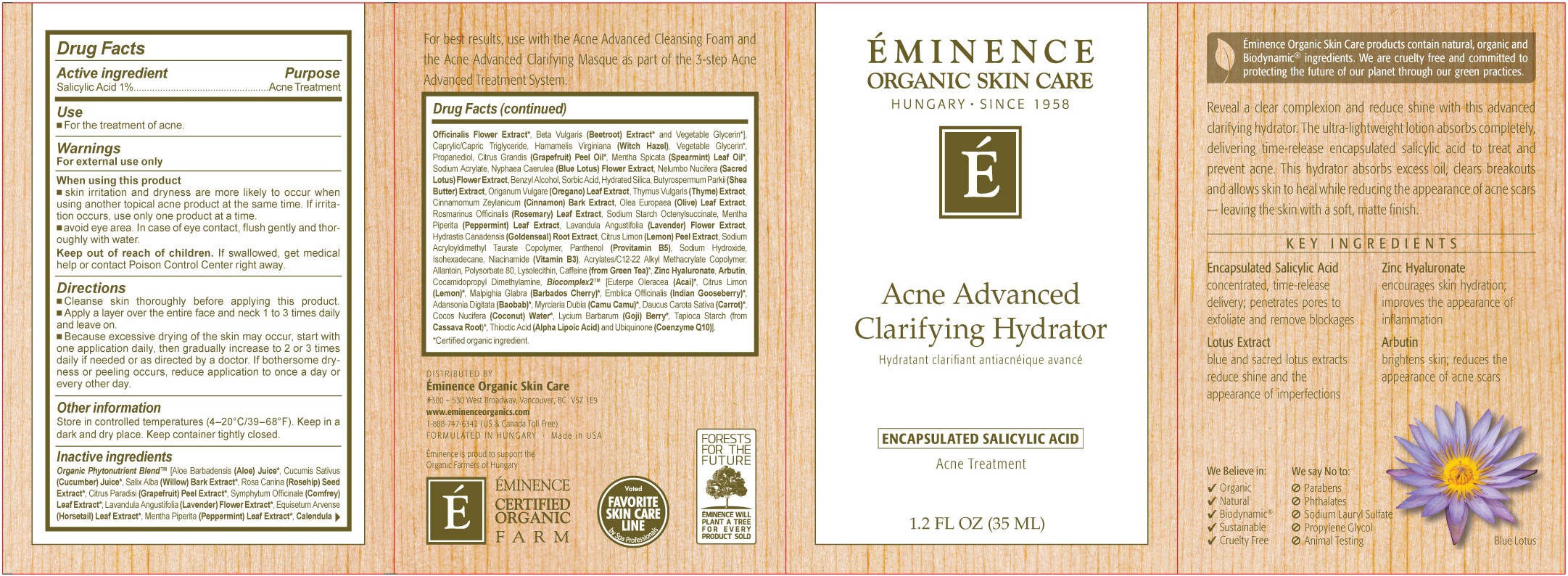 DRUG LABEL: Acne Advanced Treatment System
NDC: 15751-3000 | Form: KIT | Route: TOPICAL
Manufacturer: Eminence Organic Skin Care Ltd.
Category: otc | Type: HUMAN OTC DRUG LABEL
Date: 20231202

ACTIVE INGREDIENTS: SALICYLIC ACID 10 mg/1 mL; SALICYLIC ACID 5 mg/1 mL; SALICYLIC ACID 10 mg/1 mL
INACTIVE INGREDIENTS: ALOE; CUCUMBER; ROSA MOSCHATA OIL; GRAPEFRUIT; SYMPHYTUM UPLANDICUM LEAF; PEPPERMINT; CALENDULA OFFICINALIS FLOWER; BETA VULGARIS; GLYCERIN; DECYL GLUCOSIDE; SODIUM COCOYL GLUTAMATE; SPEARMINT; CAPRYLYL GLYCOL; TOCOPHEROL; DEXPANTHENOL; THYME; CINNAMON; OLIVE OIL; ROSEMARY; COCAMIDOPROPYL DIMETHYLAMINE; GOLDENSEAL; LEMON; ETHYLHEXYLGLYCERIN; GREEN TEA LEAF; SODIUM PYRROLIDONE CARBOXYLATE; ARBUTIN; ACAI; CARROT; COCONUT; STARCH, TAPIOCA; THIOCTIC ACID; UBIDECARENONE; PEPPERMINT; ALOE; CUCUMBER; ROSA MOSCHATA OIL; GRAPEFRUIT; SYMPHYTUM UPLANDICUM LEAF; CALENDULA OFFICINALIS FLOWER; BETA VULGARIS; GLYCERIN; SOYBEAN OIL; BENZYL ALCOHOL; SUNFLOWER OIL; SORBIC ACID; SODIUM POLYACRYLATE (2500000 MW); SPEARMINT; COCAMIDOPROPYL DIMETHYLAMINE; SULFUR; BASIL OIL; XANTHAN GUM; MONTMORILLONITE; SODIUM PYRROLIDONE CARBOXYLATE; POLYSORBATE 20; EUCALYPTUS OIL; VITAMIN A PALMITATE; ACAI; CARROT; COCONUT; STARCH, TAPIOCA; THIOCTIC ACID; UBIDECARENONE; ALOE; CUCUMBER; ROSA MOSCHATA OIL; GRAPEFRUIT; SYMPHYTUM UPLANDICUM LEAF; PEPPERMINT; CALENDULA OFFICINALIS FLOWER; BETA VULGARIS; GLYCERIN; MEDIUM-CHAIN TRIGLYCERIDES; HAMAMELIS VIRGINIANA ROOT BARK/STEM BARK; PROPANEDIOL; CITRUS MAXIMA FRUIT RIND OIL; SPEARMINT; SODIUM ACRYLATE; OREGANO; THYME; CINNAMON; OLIVE OIL; ROSEMARY; GOLDENSEAL; LEMON; DEXPANTHENOL; SODIUM HYDROXIDE; ISOHEXADECANE; NIACIN; ALLANTOIN; POLYSORBATE 80; LYSOPHOSPHATIDYLCHOLINE, SOYBEAN; GREEN TEA LEAF; ARBUTIN; COCAMIDOPROPYL DIMETHYLAMINE; SOYBEAN OIL; BENZYL ALCOHOL; SUNFLOWER OIL; SORBIC ACID; SODIUM POLYACRYLATE (2500000 MW); ACAI; CARROT; COCONUT; STARCH, TAPIOCA; THIOCTIC ACID; UBIDECARENONE

Acne Advanced Treatment System

Active ingredient

Salicylic Acid 1%

Purpose

Acne Treatment

Use

- For the treatment of acne.

Warnings

For external use only

When using this product

- Skin irritation and dryness are more likely to occur when using another topical acne product at the same time. If irritation occurs, use only one product at a time.
- Avoid eye area. In case of eye contact, flush gently and thoroughly with water.

Keep out of reach of children.

If swallowed, get medical help or contact Poison Control Center right away.

Direcitons

- Use 1 to 3 times daily.
- Pump a small amount of product to transform the liquid into a lightweight foam. Apply to skin and massage gently with fingertips in a circular motion covering the face and neck. Rinse thoroughly and pat dry.
- Because excessive drying of the skin may occur, strar with one application daily, then gradually increase to 2 ot 3 times daily if needed or as directed by a doctor. if bothersome dryness or peeling occurs, reduce application to once a day or every other day.

Other information

Store in controlled temperatures (4-20°C/39-68°F). Keep in a dark and dry place. Keep container tightly closed.

Inactive ingredients

Organic Phytonutrient Blend (Aloe Barbadensis (Aloe) Juice, Cucumis Sativus (Cucumber) Juice, Salix Alba (Willow) Bark Extract, Rosa Canina (Rosehip) Seed Extract, Citrus Paradisi (Grapefruit) Peel Extract, Symphytum Officinale (Comfrey) Leaf Extract, Lavandula Angustifolia (Lavender) Flower Extract, Equisetum Argense (Horsetail Leaf Extract, Mentha Piperita (Peppermint) Leaf Extract, Calendula Officinalis Flower Extract, Beta Vulgaris (Beetroot) Extract and Vegetable Glyceri], Decyl Glucoside, Sodium Cocoyl Glutamate, Citrus Grandis (Grapefruit) Peel Oil, Metha Spicata (Spearmint) Leaf Oil, Caprylyl Glycol, Tocopherol (Vitamin E), Panthenol (Provitamin B5), Thymus Vulgans (Thyme) Extract, Cinnamomum Zeylanicum (Cinnamon) Bark Extract, Ole Europaea (Olive) Leaf Extract, Rosmarinus Officinalis (Rosemary) Leaf Extract, Cocamidopropyl Dimethylamine, Mentha Piperita (Peppermint) Leaf Extract, Lavandula Angustifolia (Lavender) Flower Extract, Hydrastis Canadensis (Goldenseal) Root Extract, Citrus Limon (Lemon) Peel Extract, Ethylhexylglycerin, Caffeine (from Green Tea), Sodium PCA, Arbutin, Biocomplex2 [Euterpe Oleracea (Acai), Citrus Limon (Lemon), Malpighia Glabra (Barbados Cherry), Emblica Officinalis (Indian Gooseberry), Adansonia Digitata (Baobab), Myrciaria Dubia (Camu Camu), Daucus Carota Sativa (Carrot), Cocos Nucifera (Coconut) Water, Lycium Barbarum (Goji) Berry, Tapioca Starch (from Cassave Root), Thioctic Acid (Alpha Lipoic Acid) and Ubiquinone (Coenzyme Q10), Vegetable Glycerin. *Certified organic ingredient

Active ingredient

Salicylic Acid 0.5%

Purpose

Acne Treatment

Use

- For the treatment of acne.

Warnings

For external use only

When using this product

- Skin irritation and dryness are more likely to occur when using another topical acne product at the same time. if irritation occurs, use only one product at a time.
- Avoid eye area. In case of eye contact, flush gently and thoroughly with water.

Keep out of reach of children.

If swallowed, get medical help or contaact Poison Control Center right away.

Direcitons

- Cleanse skin thoroughly before applying this product
- Apply a small amount evenly over the entire face or as a spot treatment as desired.
- Allow to dry for 5 to 10 minutes.
- Rinse thoroughly with lukewarm water and use a face cloth if desired.
- Use weekly as a masque, or as a spot treatment up to 3 times per day. Because excessive drying of the skin may occur, start with one application daily, then gradually increase to 2 ot 3 times daily if needed or as directed by a doctor. if bothersome dryness or peeling occurs, reduce application to once a day or every other day.

Other information

Store in controlled temperatures (4-20°C/39-68°F). Keep in a dark and dry place. Keep container tightly closed. Do not use if seal under cap is broken or missing.

Inactive ingredients

Organic Phytonutrient Blend (Aloe Barbadensis (Aloe) Juice, Cucumis Sativus (Cucumber) Juice, Salix Alba (Willow) Bark Extract, Rosa Canina (Rosehip) Seed Extract, Citrus Paradisi (Grapefruit) Peel Extract, Symphytum Officinale (Comfrey) Leaf Extract, Lavandula Angustifolia (Lavender) Flower Extract, Equisetum Argense (Horsetail Leaf Extract, Mentha Piperita (Peppermint) Leaf Extract, Calendula Officinalis Flower Extract, Beta Vulgaris (Beetroot) Extract and Vegetable Glycerin], Kaolin Clay, Red Kaolin Clay, Vegetable Glycerin, Glycine Soja Soybean) Oil, Benzyl Alcohol, Helianthus Annuus (Sunflower Seed) Oil, Sorbic Acid, Polyacrylate 13, Citrus Grandis (Grapefruit) Peel Oil, Metha Spicata (Spearmint) Leaf Oil, Polysobutene, Cocamidopropyl Dimethylamine, Sulfur, Ocimum Basillicum (Basil) Oil, Lavandula Angustifolia (Lavender) Flower Extract, Tocopheryl Acetate (Vitamin E), Xanthan Gum, Montmorillonite Caly, Sodium PCA, Polysorbate 20, Eucalyptus Globulus (Eucalyptus) Oil, Retinyl Palmitate (Vitamin A), Usnea Barbata (Lichen) Extract, Biocomplex2 [Euterpe Oleracea (Acai), [Euterpe Oleracea (Acai), Citrus Limon (Lemon), Malpighia Glabra (Barbados Cherry), Emblica Officinalis (Indian Gooseberry), Adansonia Digitata (Baobab), Myrciaria Dubia (Camu Camu), Daucus Carota Sativa (Carrot), Cocos Nucifera (Coconut) Water, Lycium Barbarum (Goji) Berry, Tapioca Starch (from Cassave Root), Thioctic Acid (Alpha Lipoic Acid) and Ubiquinone (Coenzyme Q10)

*Certified organic ingredient

Active ingredient

Salicylic Acid 1%

Purpose

Acne Treatment

Use

- For the treatment of acne.

Warnings

For external use only

When using this product

- Skin irritation and dryness are more likely to occur when using another topical acne product at the same time. if irritation occurs, use only one product at a time.
- avoid eye area. In case of eye contact, flush gently and thoroughly with water.

Keep out of reach of children.

If swallowed, get medical help or contaact Poison Control Center right away.

Direcitons

- Cleanse skin thoroughly before applying this product
- Apply a layer over the entire face and neck 1 to 3 times daily and leave on.
- Because excessive drying of the skin may occur, start with one application daily, then gradually increase to 2 ot 3 times daily if needed or as directed by a doctor. If bothersome dryness or peeling occurs, reduce application to once a day or every other day.

Other information

Store in controlled temperatures (4-20°C/39-68°F). Keep in a dark and dry place. Keep container tightly closed.

Inactive ingredients

Organic Phytonutrient Blend (Aloe Barbadensis (Aloe) Juice, Cucumis Sativus (Cucumber) Juice, Salix Alba (Willow) Bark Extract, Rosa Canina (Rosehip) Seed Extract, Citrus Paradisi (Grapefruit) Peel Extract, Symphytum Officinale (Comfrey) Leaf Extract, Lavandula Angustifolia (Lavender) Flower Extract, Equisetum Argense (Horsetail Leaf Extract, Mentha Piperita (Peppermint) Leaf Extract, Calendula Officinalis Flower Extract, Beta Vulgaris (Beetroot) Extract and Vegetable Glycerin], Caprylic/Capric Triglyceride, Hamamelis Virginiana (Witch Hazel), Vegetable Glycerin, Propanediol, Citrus Grandis (Grapefruit) Peel Oil, Mentha Spicata (Spearmint) Leaf Oil, Sodium Acrylate, Nyphaea Caerulea (Blue Lotus) Flower Extract, Nelumbo Nucifera (Sacred Lotus) Flower Extract, Origanum Vulgare (Oregano) Leaf Extract, Thymus Vulgaris (Thyme) Extract, Cinnamomum Zeylanium (Cinnamon) Bark Extract, Olea Europaea (Olive) Leaf Extract, Rosmarinus Officinalis (Rosemary) Leaf Extract, Sodium Starch Octenylsuccinate, Mentha Piperita (Peppermint) Leaf Extract, Lavandula Angustifolia (Lavender) Flower Extract, Hydrastis Canadensis (Goldenseal) Root Extract, Citrus Limon (Lemon) Peel Extract, Sodium Acrylolydimethyl Taurate Copolymer, Panthenol (Provitamin B5), Sodium Hydroxide, Isohexadecane, Niacinamide (Vitamin B3), Acrylates/C12-22 Alkyl Methacrylate Copolymer, Allantoin, Polysorbate 80, Lysolecithin, Caffeine (from Green Tea), Zinc Hyaluronate, Arbutin, Cocamidopropyl Dimethylamine, Biocomplex2 [Euterpe Oleracea (Acai), [Euterpe Oleracea (Acai), Citrus Limon (Lemon), Malpighia Glabra (Barbados Cherry), Emblica Officinalis (Indian Gooseberry), Adansonia Digitata (Baobab), Myrciaria Dubia (Camu Camu), Daucus Carota Sativa (Carrot), Cocos Nucifera (Coconut) Water, Lycium Barbarum (Goji) Berry, Tapioca Starch (from Cassave Root), Thioctic Acid (Alpha Lipoic Acid) and Ubiquinone (Coenzyme Q10)

*Certified organic ingredient